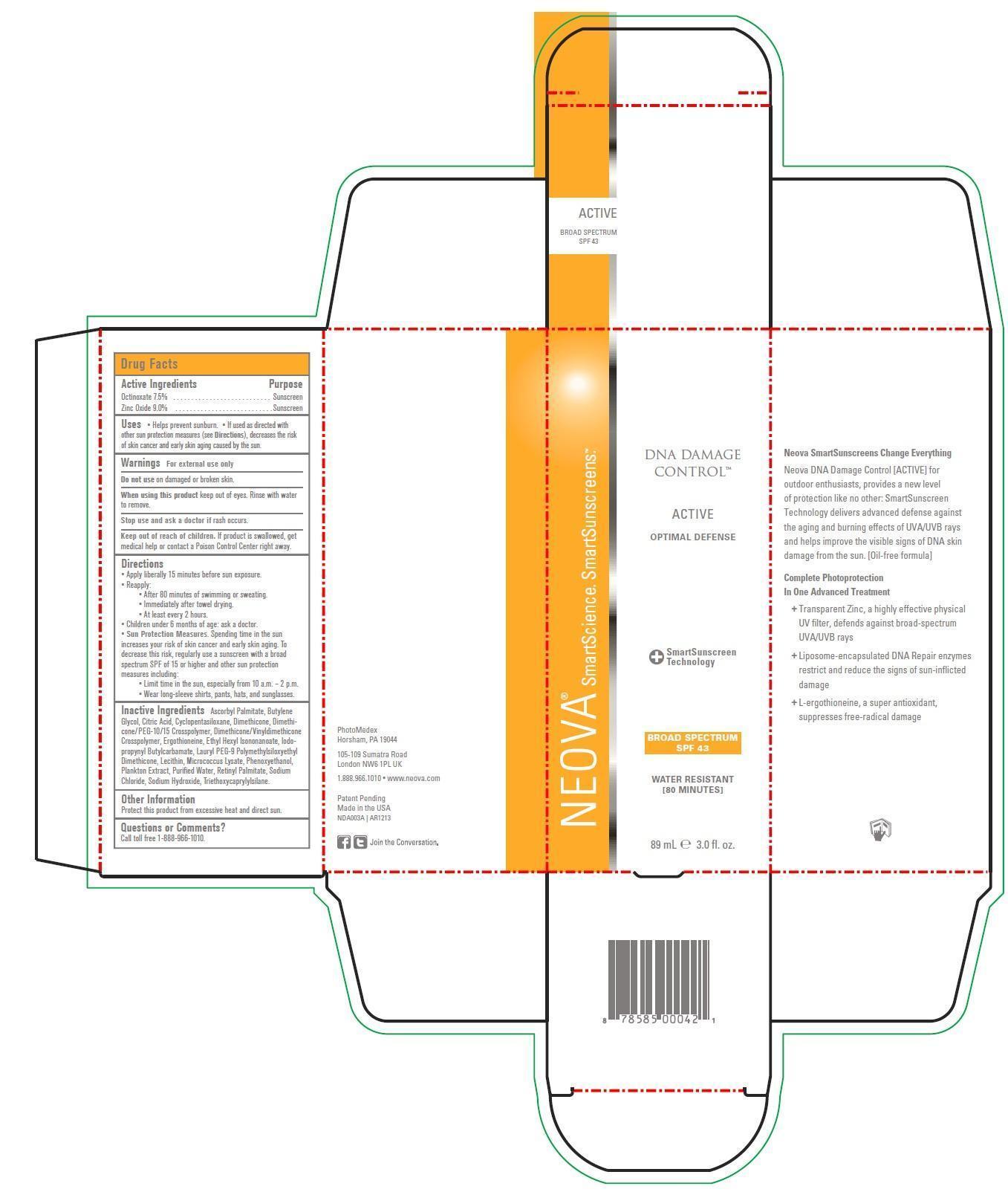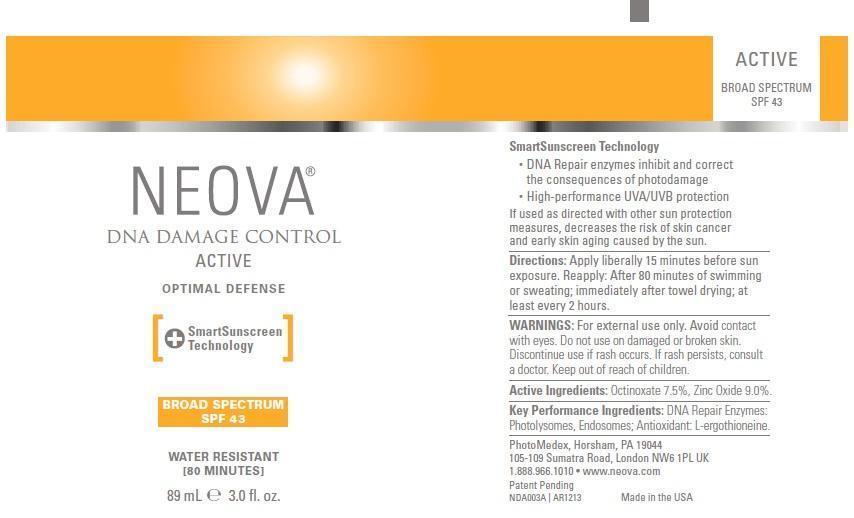 DRUG LABEL: Neova DNA Damage Control - Active
NDC: 62362-179 | Form: EMULSION
Manufacturer: PhotoMedex, Inc.
Category: otc | Type: HUMAN OTC DRUG LABEL
Date: 20140102

ACTIVE INGREDIENTS: OCTINOXATE 7.5 g/100 mL; ZINC OXIDE 9 g/100 mL
INACTIVE INGREDIENTS: ASCORBYL PALMITATE; BUTYLENE GLYCOL; CITRIC ACID MONOHYDRATE; CYCLOMETHICONE 5; DIMETHICONE; ERGOTHIONEINE; ETHYLHEXYL ISONONANOATE; IODOPROPYNYL BUTYLCARBAMATE; EGG PHOSPHOLIPIDS; PHENOXYETHANOL; WATER; VITAMIN A PALMITATE; SODIUM CHLORIDE; SODIUM HYDROXIDE; TRIETHOXYCAPRYLYLSILANE

Neova DNA Damage Control Active SPF 43 - Drug Facts

Active Ingredients

Octinoxate 7.5%, Zinc Oxide 9.0%

Purpose

Sunscreen

Uses

- Helps prevent sunburn
- If used as directed and with other sun protection measures (see Directions), decreases the risk of skin cancer and early skin again caused by the sun.

Warnings

For external use only

Do not use on damaged or broken skin.

When using this product keep out of eyes. Rinse with water to remove.

Stop use and ask a doctor if rash occurs.

Keep out of reach of children. If product is swallowed, get medical help or contact a Poison Control Center right away.

Directions

- Apply liberally 15 minutes before sun exposure.
- Reapply:

°After 80 minutes of swimming or sweating.

°Immediately after towel drying.

°At least every two hours.

- Children under 6 months of age: ask a doctor.
- Sun Protection Measures. Spending time in the sun increases your risk of skin cancer and early skin aging. To decrease this risk, regularly use a sunscreen with a broad spectrum SPF of 15 or higher and other sun protection measures including:

°Limit time in the sun, especially from 10 a.m. - 2 p.m.

°Wear long-sleeve shirts, pants, hats, and sunglasses.

Inactive Ingredients

Ascorbyl Palmitate, Butylene Glycol, Citric Acid, Cyclopentasiloxane, Dimethicone, Dimethicone/PEG-10/15 Crosspolymer, Dimethicone/Vinyldimethicone Crosspolymer, Ergothioneine, Ethyl Hexyl Isononanoate,Iodopropynyl Butylcarbamate, Lauryl PEG-9 Polymethylsiloxyethyl Dimethicone, Lecithin, Microcoous Lysate, Phenoxyethanol, Plankton Extract, Purified Water, Retinyl Palmitate, Sodium Chloride, Sodium Hydroxide, Triethanoxycaprylylsilane.

Other Information

Protect this product from excessive heat and direct sun.

Questions or Comments?

Call toll free 1-888-966-1010.

Neova DNA Damage Control Active SPF 43 3.0 fl. oz. (89mL)

DNADamageControl3ozActiveBox.jpg DNADamageControl3ozActiveLabel.jpg